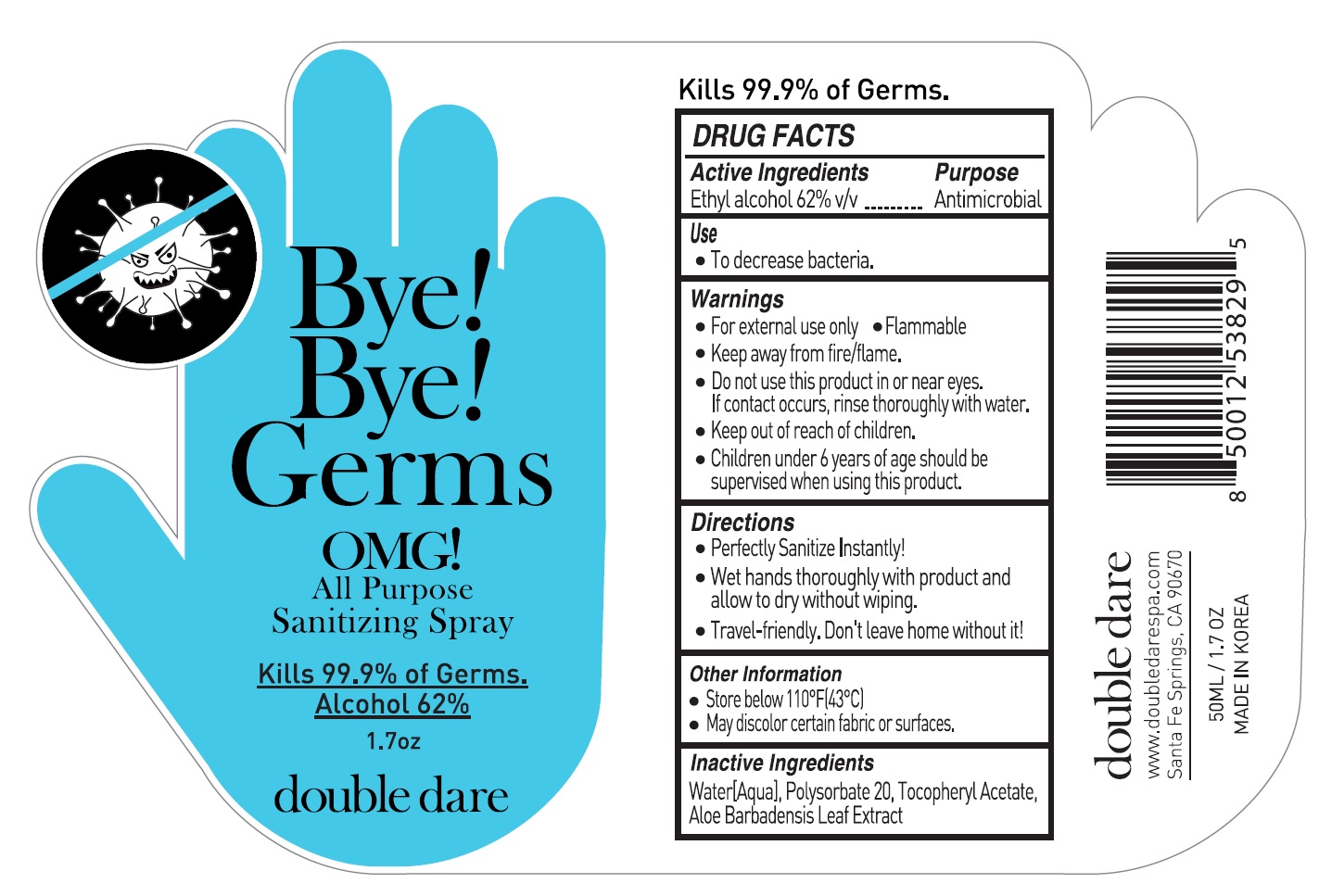 DRUG LABEL: Bye Bye Germs OMG All Purpose Sanitizing
NDC: 73724-002 | Form: SPRAY
Manufacturer: JK BEAUTY GROUP, INC.
Category: otc | Type: HUMAN OTC DRUG LABEL
Date: 20200424

ACTIVE INGREDIENTS: ALCOHOL 0.62 mg/1 mL
INACTIVE INGREDIENTS: WATER; POLYSORBATE 20; .ALPHA.-TOCOPHEROL ACETATE; ALOE VERA LEAF

Bye Bye Germs OMG All Purpose Sanitizing

Active ingredient

Ethyl alcohol 62% v/v

Purpose

Antimicrobial

Use

- To decrease bacteria

Warnings

Flammable. Keep away from fire or flame.

For external use only

When using this product do not use in or near the eyes. In case of contact, rinse eyes thoroughly with water.

Stop use and ask a doctor if irritation or rash appears and lasts

Keep out of reach of children.

Other information

- Store below 110°F (43°C)
- May discolor certain fabrics or surfaces

Directions

Perfectly Sanitize Instantly!
Wet hands thoroughly with product and allow to dry without wiping
Travel-friendly. Don't leave home without it!

Inactive ingredients

Water (Aqua), Polysorbate 20, Tocopheryl QAcetate, Aloe Barbadensis Leaf Extract